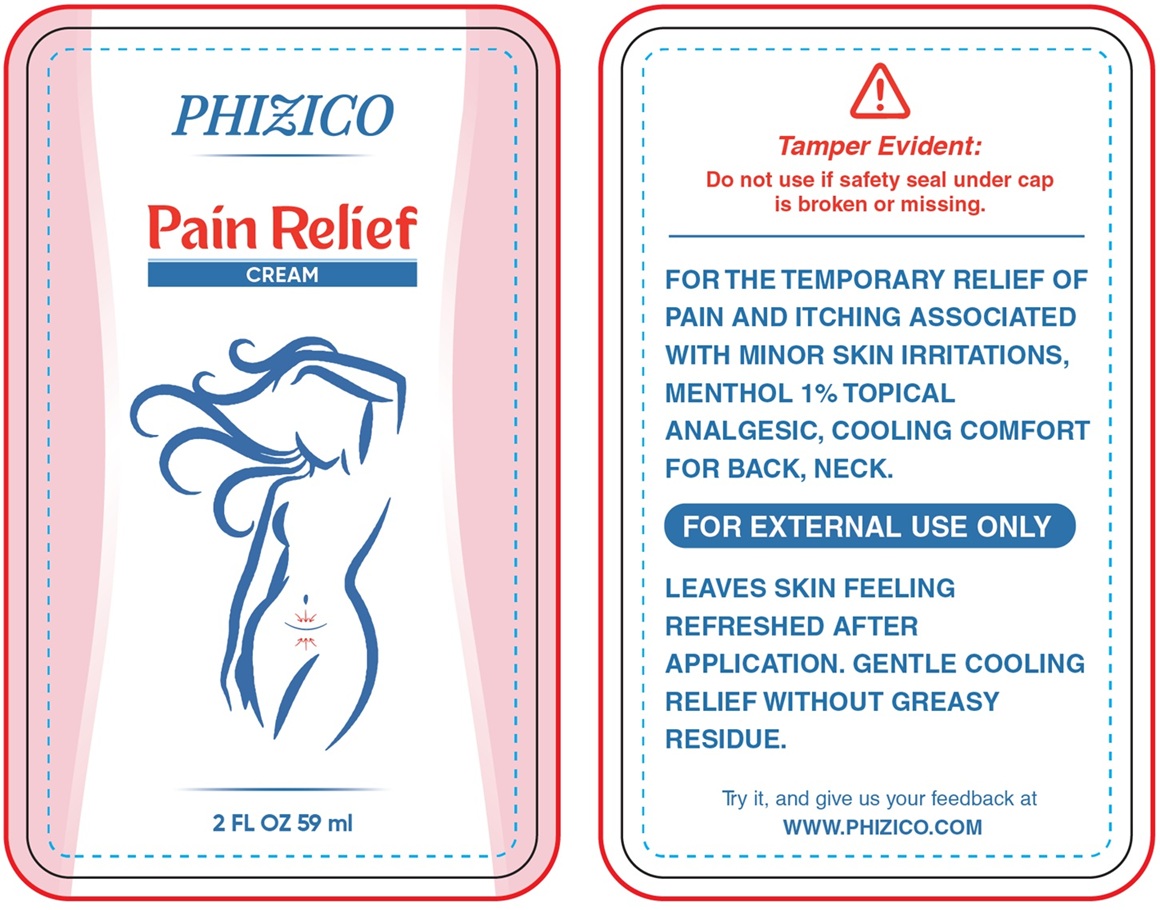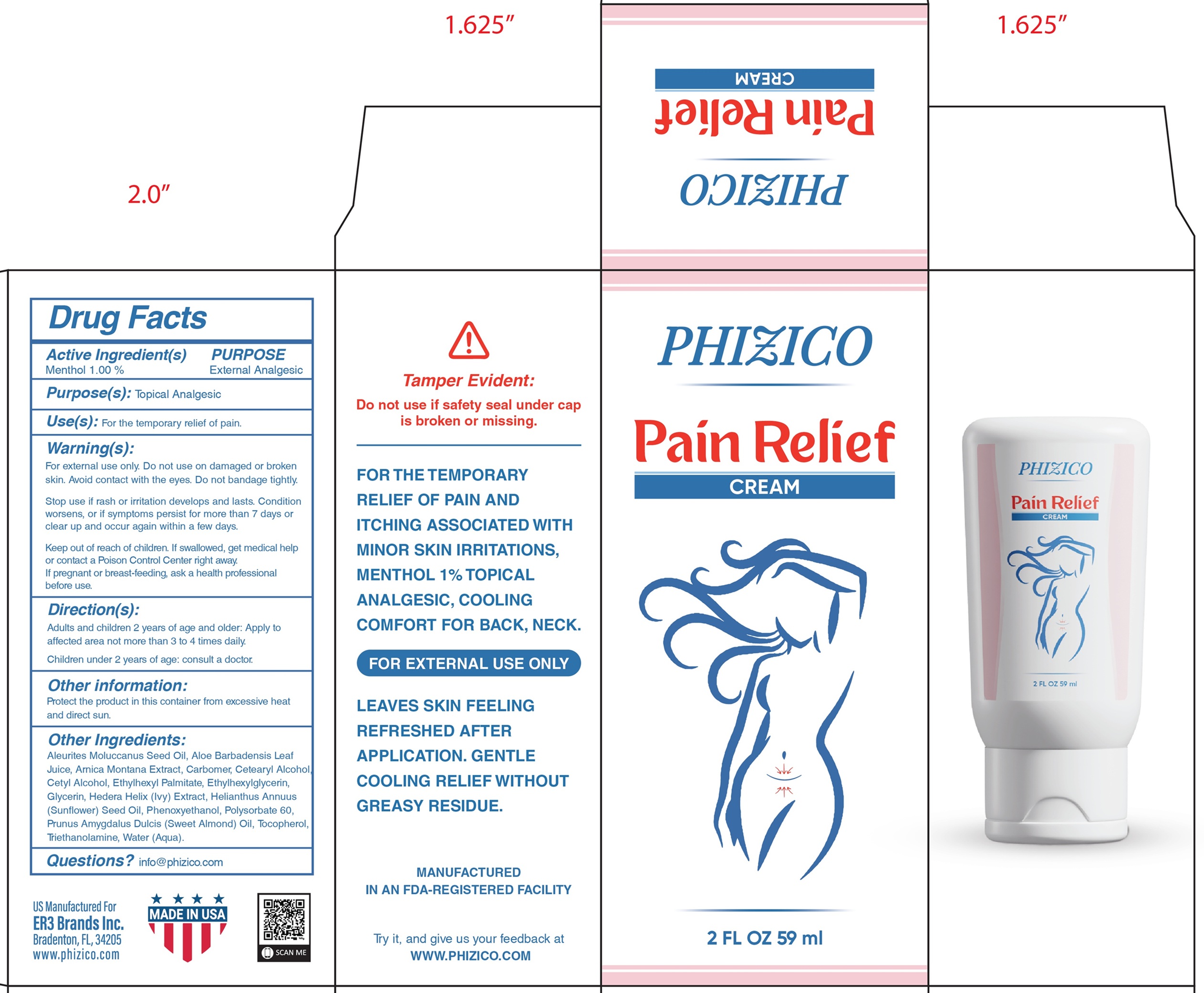 DRUG LABEL: PHIZICO Pain Relief
NDC: 85832-621 | Form: CREAM
Manufacturer: ER3 BRANDS INC.
Category: otc | Type: HUMAN OTC DRUG LABEL
Date: 20250625

ACTIVE INGREDIENTS: MENTHOL 10 mg/1 mL
INACTIVE INGREDIENTS: KUKUI NUT OIL; ALOE VERA LEAF JUICE; ARNICA MONTANA WHOLE; CARBOMER HOMOPOLYMER, UNSPECIFIED TYPE; CETOSTEARYL ALCOHOL; CETYL ALCOHOL; ETHYLHEXYL PALMITATE; ETHYLHEXYLGLYCERIN; GLYCERIN; HEDERA HELIX TOP; SUNFLOWER OIL; PHENOXYETHANOL; POLYSORBATE 60; ALMOND OIL; TOCOPHEROL; TROLAMINE; WATER

PHIZICO Pain Relief Cream

Active Ingredient(s)

Menthol 1.00%

PURPOSE

External Analgesic

Use(s):

For the temporary relief of pain.

Warning(s):

For external use only.

Do not use

on damaged or broken skin. Avoid contact with the eyes. Do not bandage tightly.

Stop use if

rash or irritation develops and lasts. Condition worsens, or if symptoms persist for more than 7 days or clear up and occur again within a few days.

Keep out of reach of children.

If swallowed, get medical help or contact a Poison Control Center right away.

If pregnant or breast-feeding,

ask a health professional before use.

Direction(s):

Adults and children 2 years of age and older: Apply to affected area not more than 3 to 4 times daily.

Children under 2 years of age: consult a doctor.

Other information:

Protect the product in this container from excessive heat and direct sun.

Other Ingredients:

Aleurites Moluccanus Seed Oil, Aloe Barbadensis Leaf Juice, Arnica Montana Extract, Carbomer, Cetearyl Alcohol, Cetyl Alcohol, Ethylhexyl Palmitate, Ethylhexylglycerin, Glycerin, Hedera Helix (lvy) Extract, Helianthus Annuus (Sunflower) Seed Oil, Phenoxyethanol, Polysorbate 60, Prunus Amygdalus Dulcis (Sweet Almond) Oil, Tocopherol, Triethanolamine, Water (Aqua).

Questions?

info@phizico.com